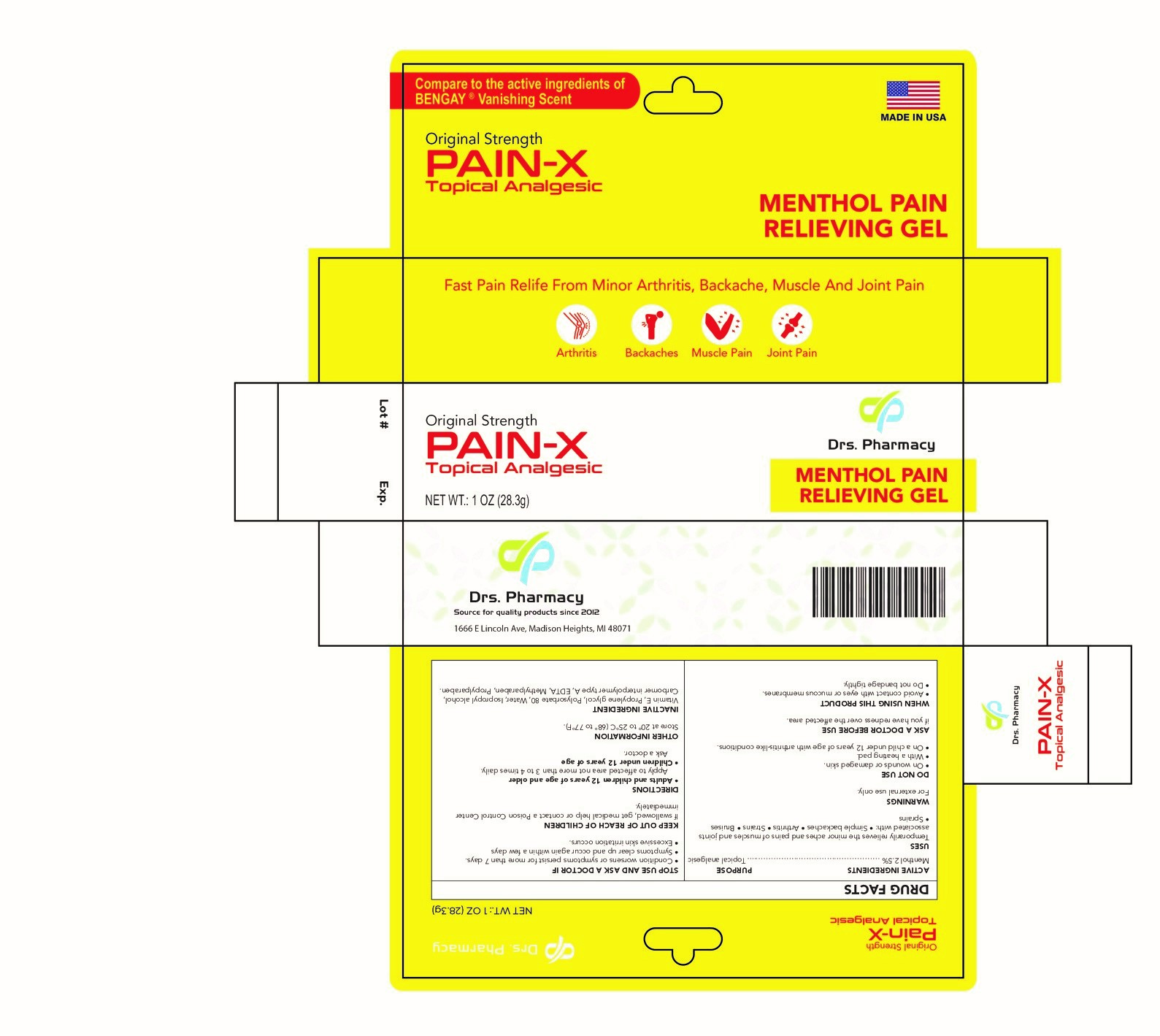 DRUG LABEL: PAIN-X
NDC: 80489-003 | Form: GEL
Manufacturer: OL PHARMA TECH,LLC
Category: otc | Type: HUMAN OTC DRUG LABEL
Date: 20250109

ACTIVE INGREDIENTS: MENTHOL, UNSPECIFIED FORM 25 mg/1 g
INACTIVE INGREDIENTS: CARBOMER INTERPOLYMER TYPE A (55000 CPS); PROPYLPARABEN; METHYLPARABEN; POLYSORBATE 80; EDETATE DISODIUM; ISOPROPYL ALCOHOL; PROPYLENE GLYCOL; .ALPHA.-TOCOPHEROL; WATER

Active ingredient

Menthol 2.5%

Purpose

Topical analgesic

Uses

temporarily relieves the minor aches and pains of muscles and joints associated with:

- simple backaches
- arthritis
- strains
- bruises
- sprains

Warnings

for external use only

Do not use

- on wounds or damaged skin
- with a heating pad
- on a child under 12 years of age with arthritis-like conditions

Ask a doctor before use if you have redness over the affected area.

When using this product

- avoid contact with eyes or mucous membranes
- do not bandage tightly

Stop use and ask a doctor if

- condition worsens or symptoms persist for more than 7 days
- symptoms clear up and occur again within a few days
- excessive skin irritation occurs

Keep out of reach of children. If swallowed, get medical help or contact a Poison Control Center immediately.

Directions

- adults and children 12 years of age and older: apply to affected area not more than 3 to 4 times daily
- children under 12 years of age: ask a doctor

Other information

- store at 20° to 25°C (68° to 77°F)

Inactive ingredients

Vitamin E, Propylene glycol,Polysorbate 80,Water, Isopropyl alcohol,Carbomer interpolymer typ A, edta, Methylparaben, Propylparaben.

Questions

www.drspharmacyusa.com